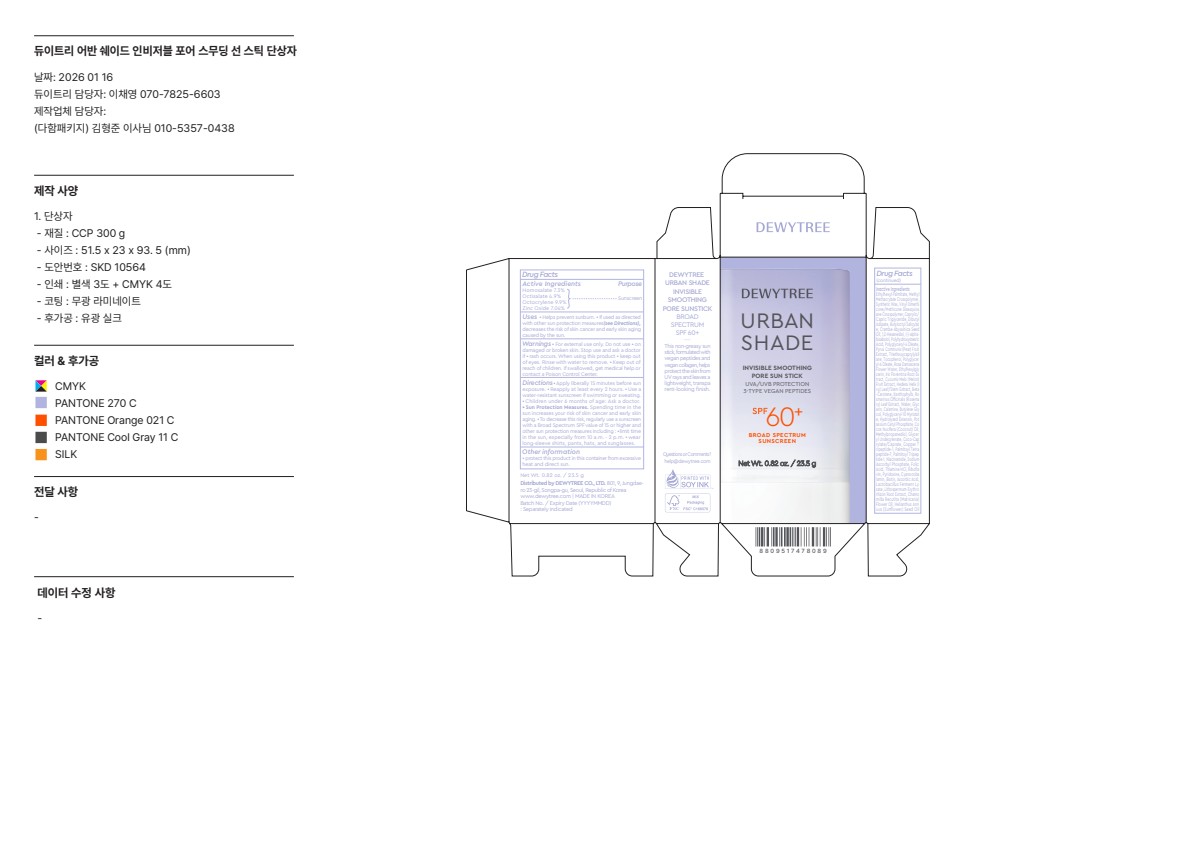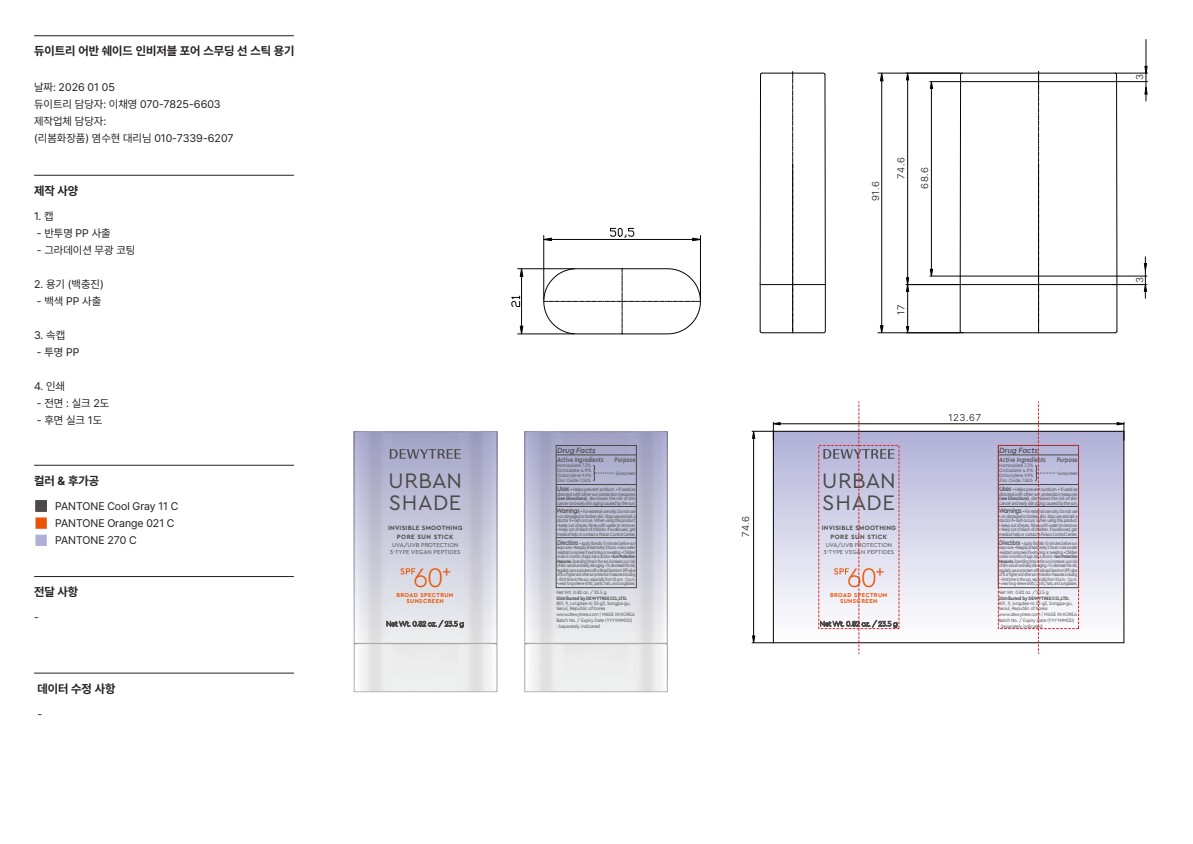 DRUG LABEL: DEWYTREE URBAN SHADE INVISIBLE SMOOTHING PORE SUNSTIC SUNSTICK
NDC: 73071-102 | Form: STICK
Manufacturer: DEWYTREE CO. ,LTD
Category: otc | Type: HUMAN OTC DRUG LABEL
Date: 20260120

ACTIVE INGREDIENTS: OCTOCRYLENE 9.9 g/23.5 g; HOMOSALATE 7.3 g/23.5 g; OCTISALATE 4.9 g/23.5 g; ZINC OXIDE 7.04 g/23.5 g
INACTIVE INGREDIENTS: NIACINAMIDE; METHYLPROPANEDIOL; POLYGLYCERYL-6 OLEATE; HELIANTHUS ANNUUS (SUNFLOWER) SEED OIL; THIAMINE HCL; PALMITOYL TETRAPEPTIDE-7; RIBOFLAVIN; CYANOCOBALAMIN; ASCORBIC ACID; PYRIDOXINE; WATER; BUTYLENE GLYCOL; POLYGLYCERYL-10 MYRISTATE; POTASSIUM CETYL PHOSPHATE; ROSMARINUS OFFICINALIS (ROSEMARY) LEAF POWDER; COCOS NUCIFERA (COCONUT) OIL; PALMITOYL TRIPEPTIDE-1; COCO-CAPRYLATE/CAPRATE; GLYCERYL MONOUNDECYLENATE; FOLIC ACID; BIOTIN; HYDROLYZED PORCINE COLLAGEN (ENZYMATIC; 3000 MW); SODIUM ASCORBYL PHOSPHATE; GLYCERIN; COPPER TRIPEPTIDE-1; ETHYLHEXYL PALMITATE; METHYL METHACRYLATE/GLYCOL DIMETHACRYLATE CROSSPOLYMER; PARAFFIN; VINYL DIMETHICONE/METHICONE SILSESQUIOXANE CROSSPOLYMER; CAPRYLIC/CAPRIC TRIGLYCERIDE; DIBUTYL ADIPATE; BUTYLOCTYL SALICYLATE; CRAMBE ABYSSINICA SEED OIL; 1,2-HEXANEDIOL; BISABOLOL; POLYHYDROXYSTEARIC ACID (2300 MW); POLYGLYCERYL-4 OLEATE; PYRUS COMMUNIS (PEAR) FRUIT; TRIETHOXYCAPRYLYLSILANE; .ALPHA.-TOCOPHEROL, DL-; ROSA DAMASCENA FLOWER OIL; ETHYLHEXYLGLYCERIN; IRIS FLORENTINA ROOT; MUSKMELON; HEDERA HELIX LEAF; LITHOSPERMUM ERYTHRORHIZON ROOT; CHAMOMILE FLOWER OIL; BETA CAROTENE; LUTEIN

73071-102 DEWYTREE URBAN SHADE INVISIBLE SMOOTHING PORE SUNSTIC SUNSTICK

ACTIVE INGREDIENT

Homosalate 7.3%

Octisalate 4.9%

Octocrylene 9.9%

Zinc Oxide 7.04%

PURPOSE

Sunscreen

INDICATIONS AND USAGE

■ Helps prevent sunburn. ■ if used as directed with other sun protection measures (see Directions), decreases the risk of skin cancer and early skin aging caused by the sun.

WARNINGS

• For external use only.

Do not use ■ on damaged or broken skin.

Stop use and ask a doctor if ■ rash occurs.

When using this product ■ keep out of eyes. Rinse with water to remove.

■ Keep out of reach of children. If swallowed, get medical help or contact a Poison Control Center.

Directions

■ Apply liberally 15 minutes before sun exposure. ■ Reapply at least every 2 hours. ■ Children under 6 months of age: Ask a doctor. ■ Sun Protection Measures.Spending time in the sun increases your risk of skin cancer and early skin aging. ■ To decrease this risk, regularly use a sunscreen with a Broad Spectrum SPF value of 15 or higher and other sun protection measures including: ■ limit time in the sun, especially from 10a.m.-2 p.m. wear long-sleeve shirts, pants, hats, and sunglasses.

OTHER SAFETY INFORMATION

■ protect this product in this container from excessive heat and direct sun.

INACTIVE INGREDIENT

Ethylhexyl Palmitate, Methyl Methacrylate Crosspolymer, Synthetic Wax, Vinyl Dimethi cone/Methicone Silsesquiox ane Crosspolymer, Caprylic/ Capric Triglyceride, Dibutyl Adipate, Butyloctyl Salicylat e, Crambe Abyssinica Seed Oil, 1,2-Hexanediol, Alpha-Bi sabolol, Polyhydroxystearic Acid, Polyglyceryl-4 Oleate, Pyrus Communis (Pear) Fruit Extract, Triethoxycaprylylsil ane, Tocopherol, Polyglycer yl-6 Oleate, Rosa Damascena Flower Water, Ethylhexylgly cerin, Iris Florentina Root Ex tract, Cucumis Melo (Melon) Fruit Extract, Hedera Helix (I vy) Leaf/Stem Extract, Beta -Carotene, Xanthophylls, Ro smarinus Ofﬁcinalis (Rosema ry) Leaf Extract, Water, Glyc erin, Calamine, Butylene Gly col, Polyglyceryl-10 Myristat e, Hydrolyzed Extensin, Pot assium Cetyl Phosphate, Co cos Nucifera (Coconut) Oil, Methylpropanediol, Glycer yl Undecylenate, Coco-Cap rylate/Caprate, Copper T ripeptide-1, Palmitoyl Tetra peptide-7, Palmitoyl Tripep tide-1, Niacinamide, Sodium Ascorbyl Phosphate, Folic Acid, Thiamine HCl, Riboﬂa vin, Pyridoxine, Cyanocoba lamin, Biotin, Ascorbic Acid, Lactobacillus Ferment Ly sate, Lithospermum Erythro rhizon Root Extract, Chamo milla Recutita (Matricaria) Flower Oil, Helianthus Ann uus (Sunﬂower) Seed Oil